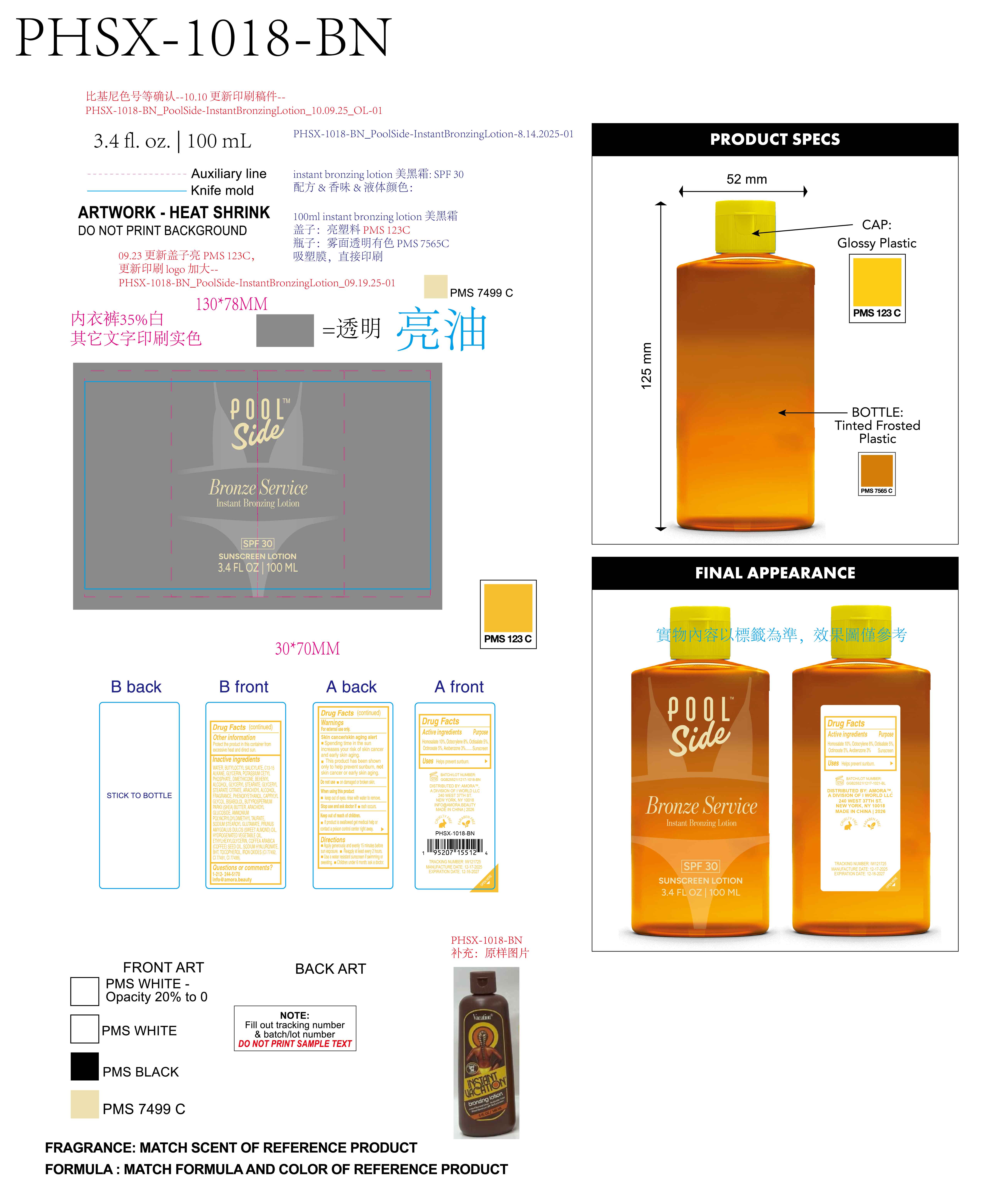 DRUG LABEL: Poolside Bronze Service Instant bronzing lotion. SPF30
NDC: 85161-156 | Form: LOTION
Manufacturer: Longway Technology(Guangzhou)Co.,Ltd.
Category: otc | Type: HUMAN OTC DRUG LABEL
Date: 20251204

ACTIVE INGREDIENTS: OCTINOXATE 0.05 g/1 mL; OCTOCRYLENE 0.08 g/1 mL; OCTISALATE 0.05 g/1 mL; HOMOSALATE 0.1 g/1 mL; AVOBENZONE 0.03 g/1 mL
INACTIVE INGREDIENTS: POTASSIUM CETYL PHOSPHATE; AMMONIUM POLYACRYLOYLDIMETHYL TAURATE; CI 77499; CI 77491; CAPRYLYL GLYCOL; BISABOLOL; DIMETHICONE; HYDROGENATED SOYBEAN OIL; ARACHIDYL ALCOHOL; PRUNUS AMYGDALUS DULCIS (SWEET ALMOND) OIL; COFFEA ARABICA (COFFEE) SEED OIL; TOCOPHEROL; ETHYLHEXYLGLYCERIN; SODIUM STEAROYL GLUTAMATE; GLYCERYL STEARATE CITRATE; CI 77492; BEHENYL ALCOHOL; BUTYROSPERMUM PARKII (SHEA) BUTTER; BUTYLOCTYL SALICYLATE; GLYCERYL STEARATE; FRAGRANCE 13576; PHENOXYETHANOL; ARACHIDYL GLUCOSIDE; SODIUM HYALURONATE; BHT; GLYCERIN; WATER; C13-15 ALKANE

ACTIVE INGREDIENT

Homosalate 10%,Octocrylene 8%, Octisalate 5%,Octinoxate 5%, Avobenzone 3%

KEEP OUT OF REACH OF CHILDREN

If product is swallowed get medical help or contact a poison control center right away.

PURPOSE

Sunscreen

QUESTIONS

1-212-244-5170 info@amora.beauty

OTHER SAFETY INFORMATION

Protect the product in this container from excessive heat and direct sun.

DOSAGE AND ADMINISTRATION

Apply generously and evenly 15 minutes belore sun exposure.

Reapply at least every 2 hours.

Use a water resistant sunscreen if swimming ors weating.

Children under 6 month: ask a doctor

WARNINGS

For external use only

Skin cancer/skin aging alert

Spending time in the sun increases your risk of skin cancer and early skin aging.

This product has been shown only to help prevent sunburn, not skin cancer or early skin aging

Do not use on damaged or broken skin.

When using this product keep out of eyes. rinse with water io remove

Stop use and ask doctorif rash occurs

Keep out of reach of children.

If product is swallowed get medical help or contact a poison control center right away.

INACTIVE INGREDIENT

WATER, BUTYLOCTYL SALICYLATE, C13-15 ALKANE, GLYCERIN, POTASSIUM CETYL PHOSPHATE, DIMETHICONE, BEHENYL ALCOHOL, GLYCERYL STEARATE, GLYCERYL STEARATE CITRATE, ARACHIDYL ALCOHOL, FRAGRANCE, PHENOXYETHANOL, CAPRYLYL GLYCOL, BISABOLOL, BUTYROSPERMUM PARKII (SHEA) BUTTER, ARACHIDYL GLUCOSIDE, AMMONIUM POLYACRYLOYLDIMETHYL TAURATE, SODIUM STEAROYL GLUTAMATE, PRUNUS AMYGDALUS DULCIS (SWEET ALMOND) OIL, HYDROGENATED VEGETABLE OIL, ETHYLHEXYLGLYCERIN, COFFEA ARABICA (COFFEE) SEED OIL, SODIUM HYALURONATE, BHT, TOCOPHEROL, IRON OXIDES（CI 77492,CI 77491,CI 77499 ）

INDICATIONS AND USAGE

Helps prevent sunbum.